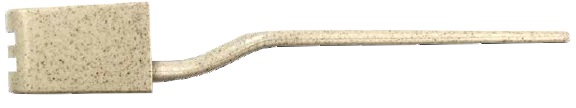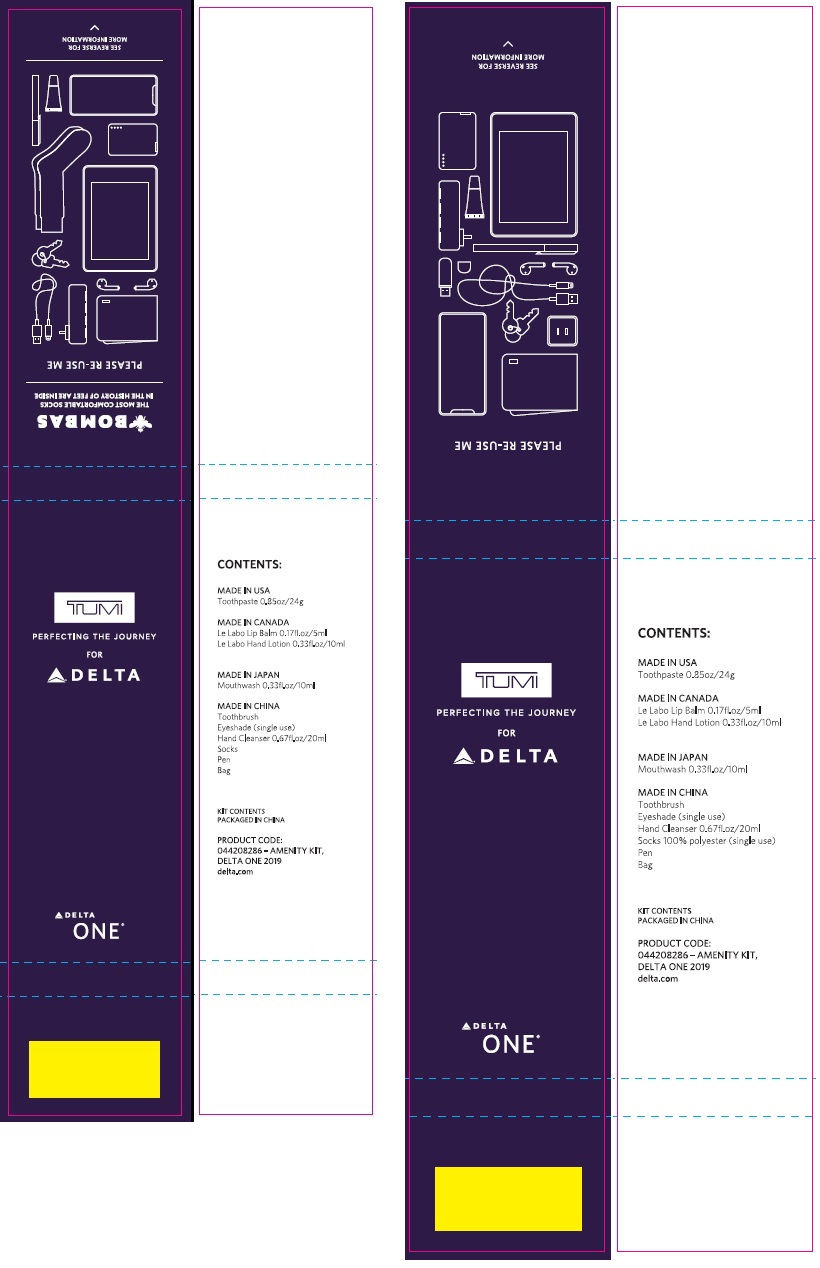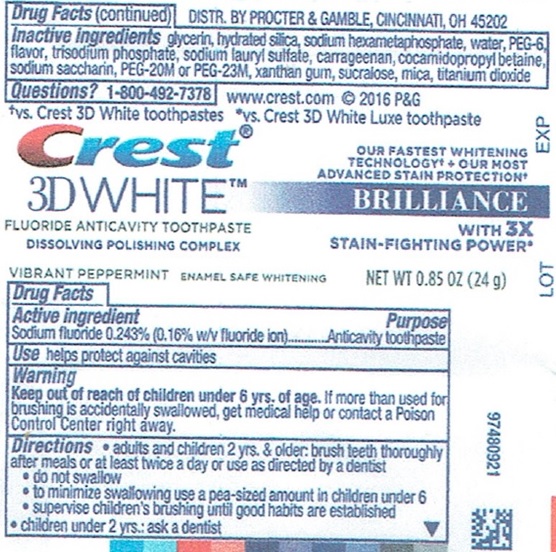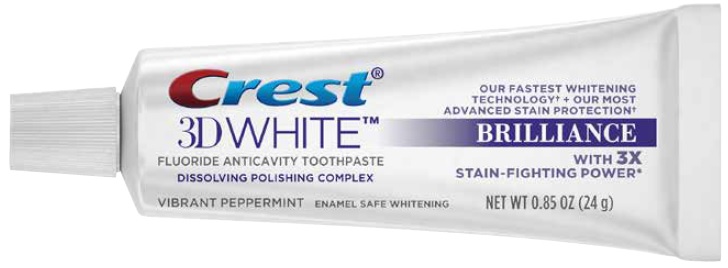 DRUG LABEL: DELTA ONE 2019 TUMI COLLINS And TUMI COLLINS BOMBAS AMENITY With Crest 3D White Brilliance
NDC: 69491-200 | Form: KIT | Route: DENTAL
Manufacturer: Buzz Export Services Pty., Ltd.
Category: otc | Type: HUMAN OTC DRUG LABEL
Date: 20211227

ACTIVE INGREDIENTS: SODIUM FLUORIDE 1.6 mg/1 g
INACTIVE INGREDIENTS: GLYCERIN; HYDRATED SILICA; HEXASODIUM HEXAMETAPHOSPHATE; WATER; POLYETHYLENE GLYCOL 300; METHYL SALICYLATE; SODIUM LAURYL SULFATE; CARRAGEENAN; COCAMIDOPROPYL BETAINE; SACCHARIN SODIUM; POLYETHYLENE OXIDE 900000; XANTHAN GUM; SUCRALOSE; MICA; TITANIUM DIOXIDE

DELTA ONE 2019 - TUMI COLLINS & TUMI COLLINS BOMBAS - AMENITY KIT With Crest 3D White Brilliance

Active ingredient

Sodium fluoride 0.243% (0.16% w/v fluoride ion)

Purpose

Anticavity toothpaste

Use

helps protect against cavities

Warning

Keep out of reach of children under 6 yrs. of age.

If more than used for brushing is accidentally swallowed, get medical help or contact a Poison Control Center right away.

Directions

- adults and children 2 yrs. & older: brush teeth thoroughly after meals or at least twice a day or use as directed by a dentist
- do not swallow
- to minimize swallowing use a pea-sized amount in children under 6
- supervise children's brushing until good habits are established
- children under 2 yrs.: ask a dentist

Inactive ingredients

glycerin, hydrated silica, sodium hexametaphosphate, water, PEG-6, flavor, trisodium phosphate, sodium lauryl sulfate, carrageenan, cocamidopropyl betaine, sodium saccharin, PEG-20M or PEG-23M, xanthan gum, sucralose, mica, titanium dioxide

Questions?

1-800-492-7378